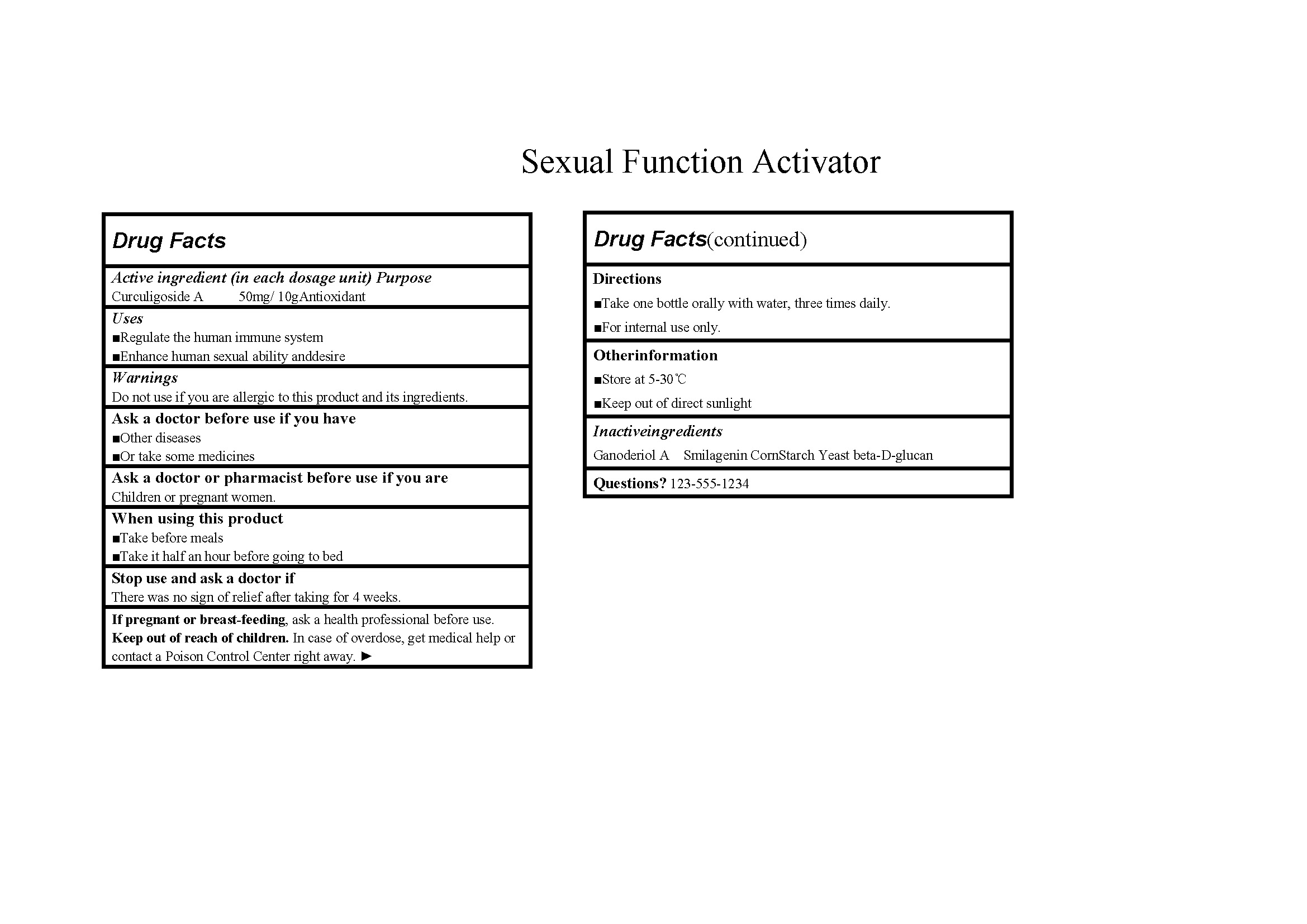 DRUG LABEL: Sexual Function Activator
NDC: 84611-102 | Form: GRANULE
Manufacturer: Sanaura Group LIMITED
Category: otc | Type: HUMAN OTC DRUG LABEL
Date: 20240815

ACTIVE INGREDIENTS: CURCULIGOSIDE A 50 mg/10 g
INACTIVE INGREDIENTS: STARCH, CORN; GANODERIOL A; SMILAGENIN; YEAST .BETA.-D-GLUCAN

Sexual Function Activator 84611-102

Active ingredient: CURCULIGOSIDE A 50mg/ 10g

Purpose: Antioxidant

INDICATIONS AND USAGE

Use to:

Regulate the human immune system;

Enhance human sexual ability anddesire

Warnings:

Do not use if you are allergic to this product and its ingredients.

Ask a doctor before use if you have:

Other diseases;

Or take some medicines

Ask a doctor or pharmacist before use if you are:

Children or pregnant women.

When using this product:

Take before meals;

Take it half an hour before going to bed

Stop use and ask a doctor if There was no sign of relief after taking for 4 weeks.

PREGNANCY OR BREAST FEEDING

If pregnant or breast-feeding, ask a health professional before use.

Keep out of reach of children. In case of overdose, get medical help or contact a Poison Control Center right away.

Directions:

Take one bottle orally with water, three times daily.

For internal use only.

Other information:

Store at 5-30℃;

Keep out of direct sunlight

INACTIVE INGREDIENT

Inactive ingredients: GANODERIOL A, SMILAGENIN, Corn Starch, YEAST .BETA.-D-GLUCAN

Questions? 123-555-1234

Label